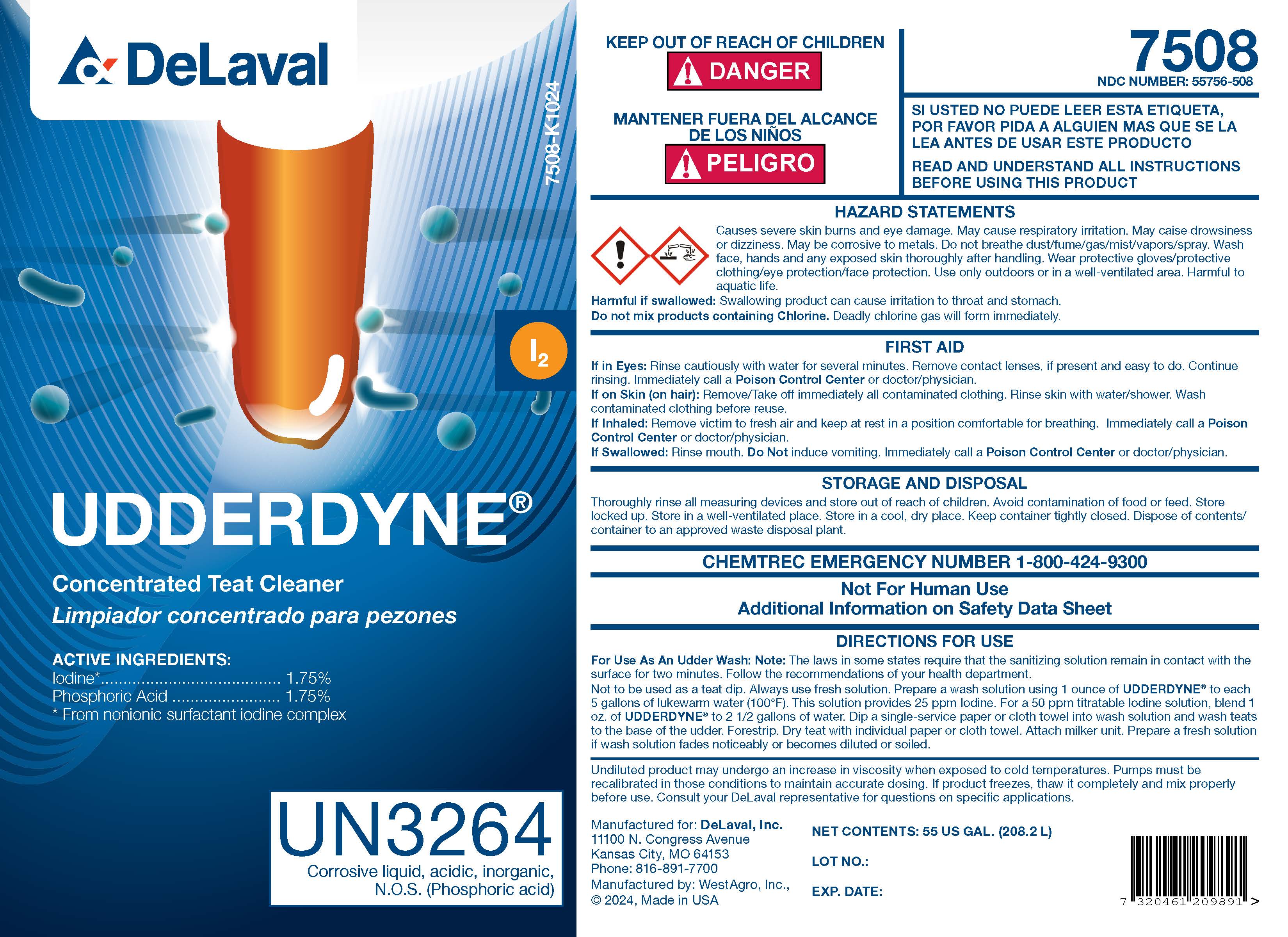 DRUG LABEL: UDDERDYNE
NDC: 55756-508 | Form: SOLUTION
Manufacturer: DeLaval, Inc.
Category: animal | Type: OTC ANIMAL DRUG LABEL
Date: 20241213

ACTIVE INGREDIENTS: IODINE 18.3 g/1 L; PHOSPHORIC ACID 18.3 g/1 L
INACTIVE INGREDIENTS: HYDROGEN IODIDE; NONOXYNOL-12; WATER

UDDERDYNE

INDICATIONS AND USAGE

Concentrated Teat Cleaner

ACTIVE INGREDIENTS:

Iodine*.............................1.75%

Phosphoric Acid..................1.75%

*From nonionic surfactant iodine complex

SAFE HANDLING WARNING

UN3264

Corrosive liquid, acidic, inorganic

N.O.S. (Phosphoric acid)

KEEP OUT OF REACH OF CHILDREN

!DANGER

USER SAFETY WARNINGS

READ AND UNDERSTAND ALL INSTRUCTIONS BEFORE USING THIS PRODUCT

HAZARD STATEMENTS

Causes severe skin burns and eye damage. May cause respiratory irritation. May cause drowsiness or dizziness. May be corrosive to metals. Do not breathe dust/fume/gas/mist/vapors/spray. Wash face, hands and any exposed skin thoroughly after handling. Wear protective gloves/protective clothing/eye protection/face protection. Use only outdoors or in a well-ventilated area. Harmful to aquatic live.

Harmful if swallowed: Swallowing product can cause irritation to throat and stomach.

Do not mix products containing Chlorine. Deadly chlorine gas will form immediately.

FIRST AID

If in Eyes: Rinse cautiously with water for several minutes. Remove contact lenses, if present and easy to do. Continue rinsing. Immediately call a Poison Control Center or doctor/physician.

If on Skin (on hair): Remove/Take off immediately all contaminated clothing. Rinse skin with water/shower. Wash contaminated clothing before reuse.

If Inhaled: Remove victim to fresh air and keep at rest in a position comfortable for breathing. Immediately call a Poison Control Center or doctor/physician.

If Swallowed: Rinse mouth. Do Not induce vomiting. Immediately call a Poison Control Center or doctor/physician.

STORAGE AND DISPOSAL

Thoroughly rinse all measuring devices and store out of reach of children. Avoid contamination of food or feed. Store locked up. Store in a well-ventilated place. Store in a cool, dry place. Keep container tightly closed. Dispose of contents/container to an approved waste disposal plant.

CHEMTREC EMERGENCY NUMBER 1-800-424-9300

WARNINGS AND PRECAUTIONS

Not for Human Use

Additional Information on Safety Data Sheet

DIRECTIONS FOR USE

For Use As An Udder Wash: Note: The laws in some states require that the sanitizing solution remain in contact with the surface for two minures. Follow the recommendations of your health department.

Not to be used as a teat dip. Always use fresh solution. Prepare a wash solution using 1 ounce UDDERDYNE® to each 5 gallons of lukewarm water (100°F). This solution provides 25 ppm Iodine. For a 50 ppm titratable Iodine solution, blend 1 oz. of UDDERDYNE to 2 1/2 gallons of water. Dip a single-service paper or cloth towel into wash solution and wash teats to the base of the udder. Forestrip. Dry teat with individual paper or cloth towel. Attach milker unit. Prepare a fresh solution if wash solution fades noticeably or becomes diluted or soiled.

WARNINGS AND PRECAUTIONS

Undiluted product may undergo an increase in viscosity when exposed to cold temperatures. Pumps must be recalibrated in those conditions to maintain accurate dosing. If product freezes, thaw it completely and mix properly before use. Consult your DeLaval representative for questions on specific applications.

NEW CONTENTS: US GAL.

LOT NO.:

EXP. DATE:

Manufactured for: DeLaval, Inc.

11100 N. Congress Avenue

Kansas City, MO 64153

Phone: 816-891-7700

Manufactured by WestAgro, Inc.,

© 2024, Made in USA

PACKAGE LABEL

Add image transcription here...